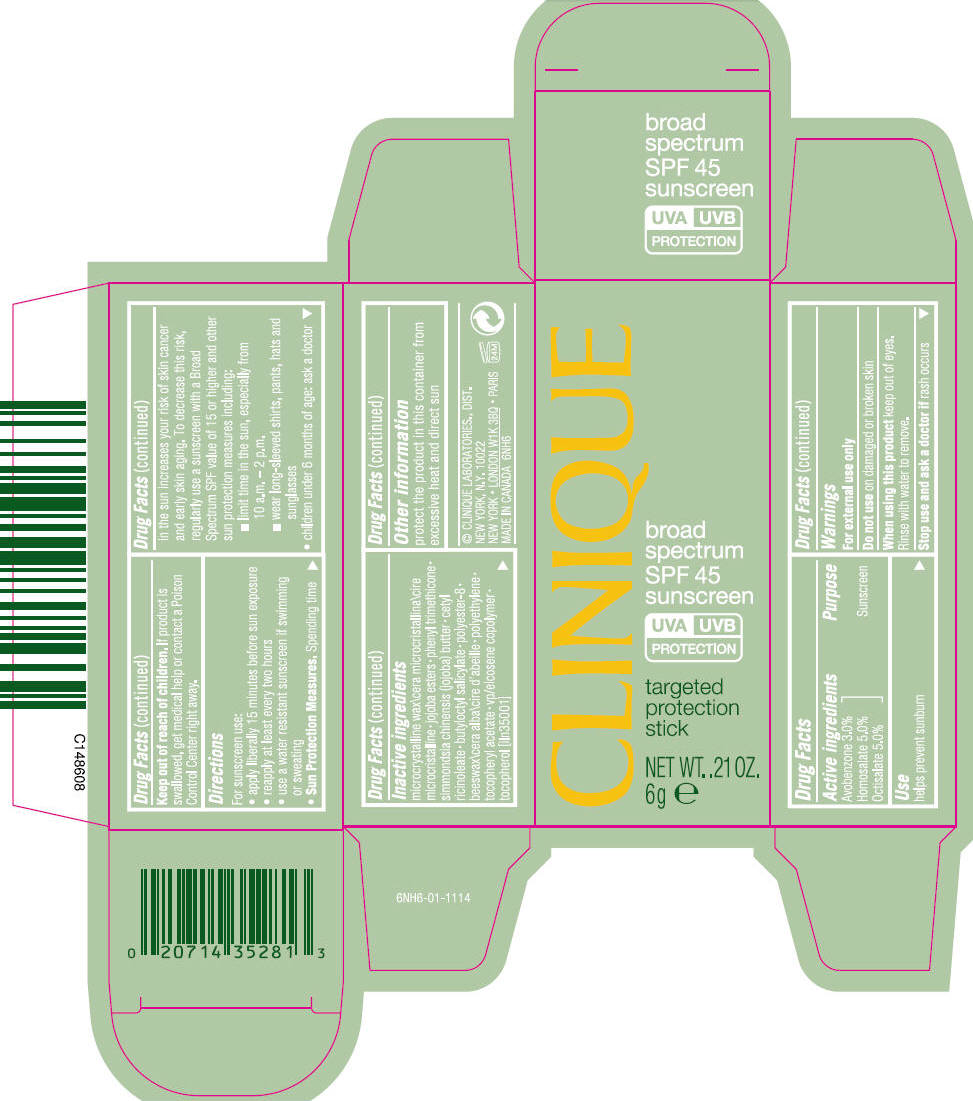 DRUG LABEL: CLINIQUE TARGETED PROTECTION SPF 45 BROAD SPECTRUM SUNSCREEN
NDC: 49527-041 | Form: STICK
Manufacturer: CLINIQUE LABORATORIES LLC
Category: otc | Type: HUMAN OTC DRUG LABEL
Date: 20241225

ACTIVE INGREDIENTS: HOMOSALATE 5 g/100 g; OCTISALATE 5 g/100 g; AVOBENZONE 3 g/100 g
INACTIVE INGREDIENTS: MICROCRYSTALLINE WAX; PHENYL TRIMETHICONE; JOJOBA BUTTER; CETYL RICINOLEATE; BUTYLOCTYL SALICYLATE; YELLOW WAX; HIGH DENSITY POLYETHYLENE; .ALPHA.-TOCOPHEROL ACETATE; TOCOPHEROL

CLINIQUE TARGETED PROTECTION STICK SPF 45 BROAD SPECTRUM SUNSCREEN

Drug Facts

Active ingredients

Avobenzone 3.0%
Homosalate 5.0%
Octisalate 5.0%

Purpose

Sunscreen

Use

helps prevent sunburn

Warnings

For external use only

Do not use on damaged or broken skin

When using this product keep out of eyes. Rinse with water to remove.

Stop use and ask a doctor if rash occurs

Keep out of reach of children. If product is swallowed, get medical help or contact a Poison Control Center right away.

Directions

For sunscreen use:

- apply liberally 15 minutes before sun exposure
- reapply at least every two hours
- use a water resistant sunscreen if swimming or sweating
- Sun Protection Measures. Spending time in the sun increases your risk of skin cancer and early skin aging. To decrease this risk, regularly use a sunscreen with a Broad Spectrum SPF value of 15 or higher and other sun protection measures including:
  - limit time in the sun, especially from 10 a.m. – 2 p.m.
  - wear long-sleeved shirts, pants, hats and sunglasses
- children under 6 months of age: ask a doctor

Inactive ingredients

microcrystalline wax\cera microcristallina\cire microcristalline • jojoba esters • phenyl trimethicone • simmondsia chinensis (jojoba) butter • cetyl ricinoleate • butyloctyl salicylate • polyester-8 • beeswax\cera alba\cire d'abeille • polyethylene • tocopheryl acetate • vp/eicosene copolymer • tocopherol [iln35001]

Other information

protect the product in this container from excessive heat and direct sun

PRINCIPAL DISPLAY PANEL - 6 g Cylinder Carton

CLINIQUE

broad
spectrum
SPF 45
sunscreen

UVA | UVB
PROTECTION

targeted
protection
stick

NET WT. .21 OZ.
6g e